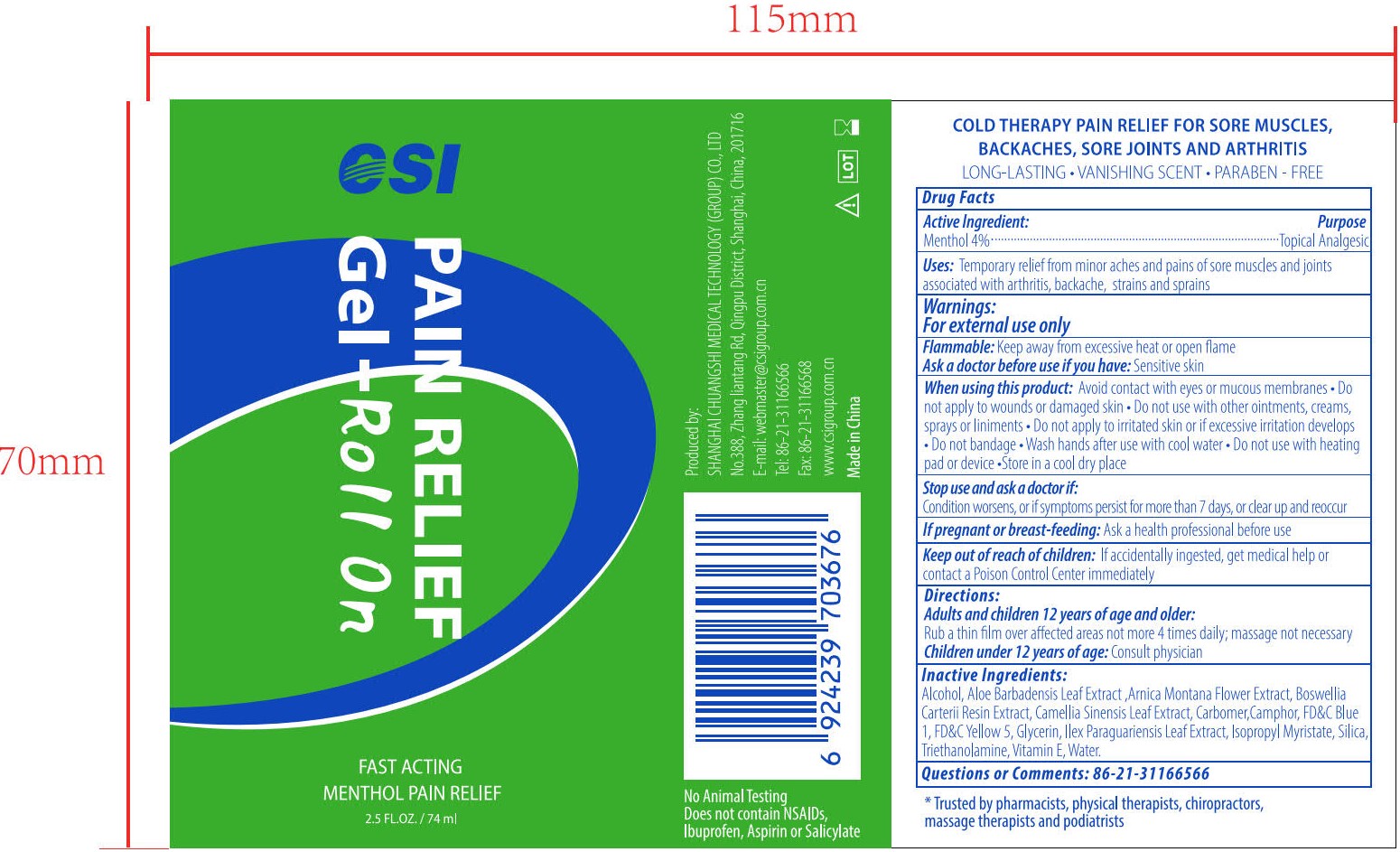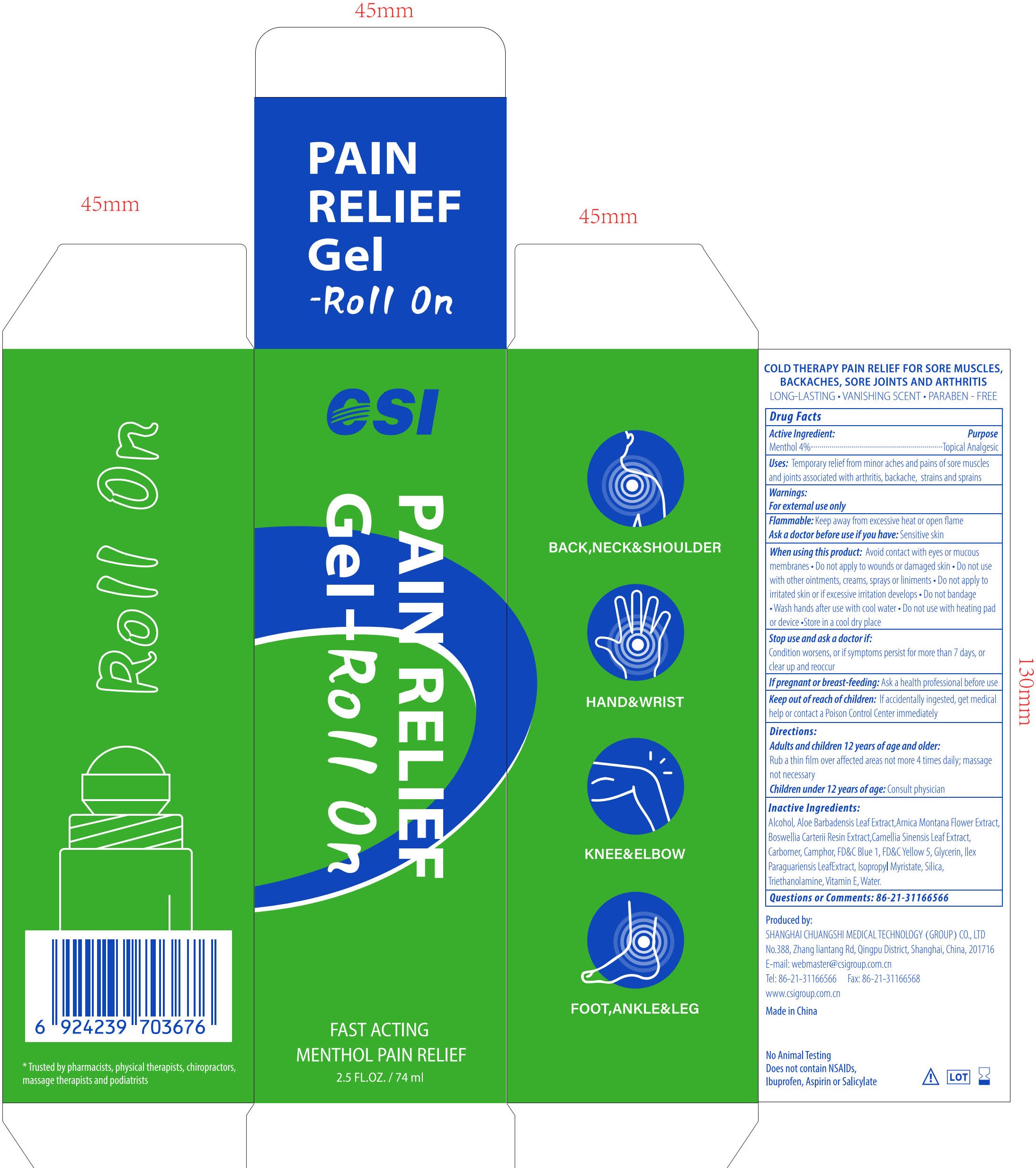 DRUG LABEL: PAIN RELIEF Gel-Roll On
NDC: 73557-333 | Form: GEL
Manufacturer: Shanghai Chuangshi Medical Technology (Group) Co., Ltd.
Category: otc | Type: HUMAN OTC DRUG LABEL
Date: 20240429

ACTIVE INGREDIENTS: MENTHOL 0.04 g/1 mL
INACTIVE INGREDIENTS: ALCOHOL 95%; TROLAMINE; WATER; SILICON DIOXIDE; ILEX PARAGUARIENSIS LEAF; ISOPROPYL MYRISTATE; .ALPHA.-TOCOPHEROL, D-; ALOE VERA LEAF; GLYCERIN; FD&C YELLOW NO. 5; FD&C BLUE NO. 1; GREEN TEA LEAF; CARBOMER HOMOPOLYMER, UNSPECIFIED TYPE; FRANKINCENSE; ARNICA MONTANA FLOWER; CAMPHOR (SYNTHETIC)

CSI, Menthol, PAIN RELIEF Gel-Roll On, 2.5 fl. oz / 74 mL, Gel, Bottle

Active Ingredient

Menthol 4.0% w/w ...... Purpose: Topical Analgesic

Purpose

Topical Analgesic

Uses

Temporary relief from minor aches and pains of sore muscles and joints associated with arthritis, backache, strains and sprains

Warnings

For external use only

Flammable

Keep away from excessive heat or open flame

Ask a doctor before use if you have

Sensitive skin

When using this product

Avoid contact with eyes or mucous membranes • Do not apply to wounds or damaged skin • Do not use with other ointments, creams, sprays or liniments • Do not apply to irritated skin or if excessive irritation develops • Do not bandage • Wash hands after use with cool water • Do not use with heating pad or device • Store in a cool dry place

DO NOT USE

• Do not apply to wounds or damaged skin • Do not use with other ointments, creams, sprays or liniments • Do not apply to irritated skin or if excessive irritation develops • Do not bandage • Do not use with heating pad or device

Stop use and ask a doctor if

Condition worsens or if symptoms persist for more than 7 days, or clear up and reoccur

If pregnant or breast-feeding

Ask a health professional before use

Keep out of reach of children

If accidentally ingested, get medical help or contact a Poison Control Center immediately

Directions

Adults and children 12 years of age and older:

Rub a thin film over affected areas not more than 4 times daily; message not necessary

Children under 12 years of age: Consult physician

Inactive Ingredients

Alcohol, Aloe Barbadensis Leaf Extract, Arnica Montana Flower Extract, Boswellia Carterii Resin Extract, Camellia Sinensis Leaf Extract, Carbomer, Camphor, FD&C Blue 1, FD&C Yellow 5, Glycerin, Ilex Paraguariensis Leaf Extract, Isopropyl Myristate, Silica, Triethanolamine, Vitamin E, Water

Questions or Comments

86-21-31166566